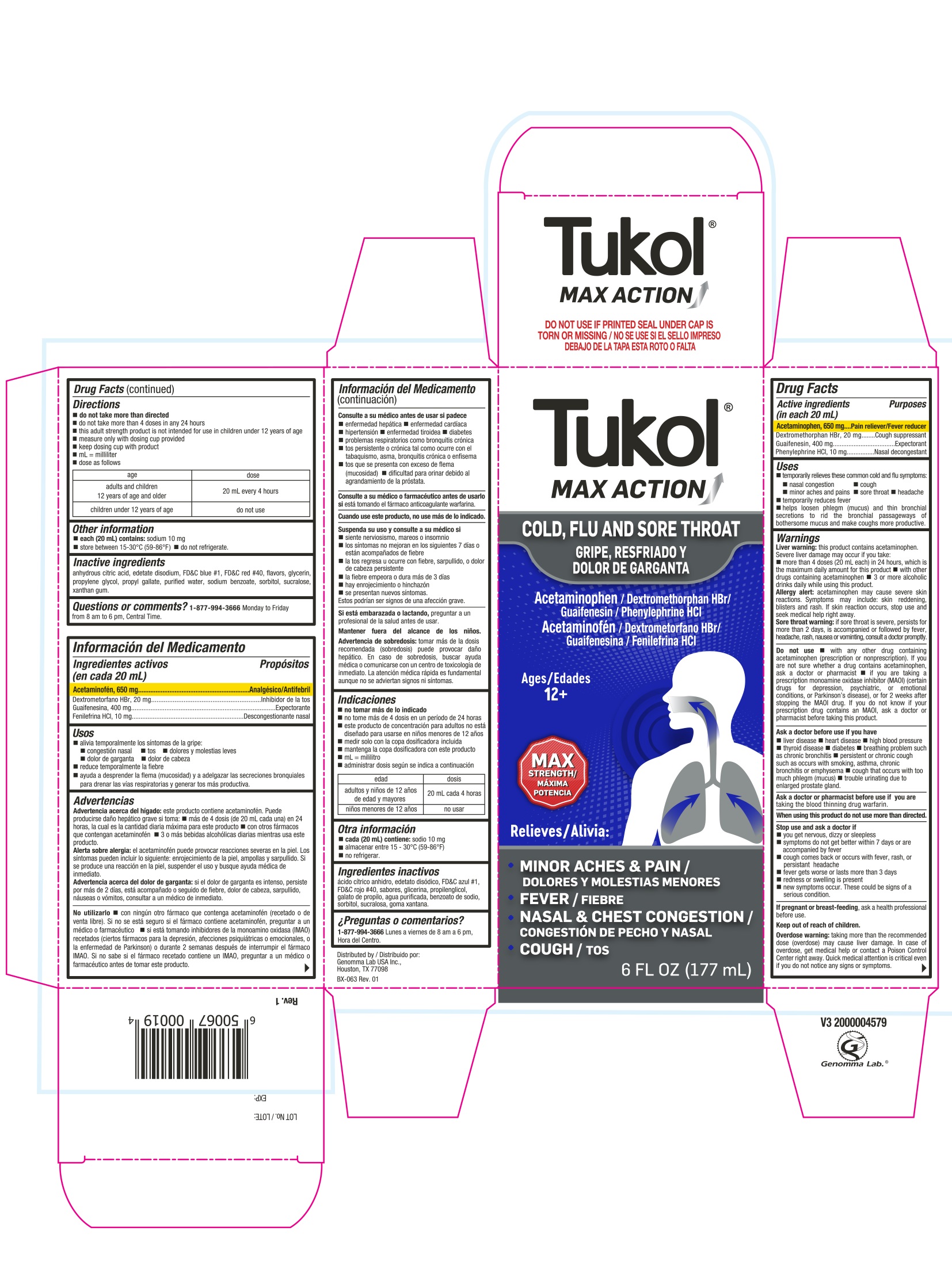 DRUG LABEL: Tukol MAX ACTION Cold, Sore Throat and Cough
NDC: 50066-516 | Form: LIQUID
Manufacturer: Genomma Lab USA, Inc
Category: otc | Type: HUMAN OTC DRUG LABEL
Date: 20241016

ACTIVE INGREDIENTS: ACETAMINOPHEN 650 mg/20 mL; DEXTROMETHORPHAN HYDROBROMIDE 20 mg/20 mL; GUAIFENESIN 400 mg/20 mL; PHENYLEPHRINE HYDROCHLORIDE 10 mg/20 mL
INACTIVE INGREDIENTS: ANHYDROUS CITRIC ACID; EDETATE DISODIUM; FD&C BLUE NO. 1; FD&C RED NO. 40; GLYCERIN; PROPYLENE GLYCOL; PROPYL GALLATE; WATER; SODIUM BENZOATE; SORBITOL; SUCRALOSE; XANTHAN GUM

Tukol Max Action Cold, Sore Throat & Cough - 516

Drug Facts Active ingredients (in each 20 mL)

Acetaminophen 650 mg
Dextromethorphan HBr 20 mg
Guaifenesin 400 mg
Phenylephrine HCL 10 mg

Purpose

Pain reliever/fever reducer
Cough suppressant
Expectorant
Nasal decongestant

Uses

- temporarily relieves these common cold and flu symptoms:
- nasal congestion
- cough
- minor aches and pains
- sore throat
- headache
- temporarily reduces fever
- helps to loosen phlegm (mucus) and thin bronchial secretions to rid the bronchial passageways of bothersome mucus and make cough more productive

Warnings

Liver warning: This product contains acetaminophen. Severe liver damage may occur if you take:

- more than 4 doses (20 mL each) in 24 hours, which is the maximum daily amount for this product
- with other drugs containing acetaminophen
- 3 or more alcoholic drinks daily while using this product

Allergy alert:Acetaminophen may cause severe skin reactions. Symptoms may include: skin reddening, blisters and rash.

If skin reaction occurs, stop use and seek medical help right away.

Sore throat warning:If sore throat is severe, persists more than 2 days, is accompanied or followed by fever, headache, rash, nausea or vomiting, consult a doctor promptly.

Do not use

- with any other drug containing acetaminophen (prescription or nonprescription). If you are not sure whether a drug contains acetaminophen, ask a doctor or pharmacist
- if you are now taking a prescription monoamine oxidase inhibitor (MAOI) (certain drugs for depression, psychiatic, or emotional conditions, or Parkinson's disease), or for 2 weeks after stopping an MAOI drug. If you do not know if your prescription drug contains an MAOI, ask a doctor or pharmacist before taking this product.

Ask a doctor before use if you have

- liver disease
- heart disease
- high blood pressure
- thyroid disease
- diabetes
- breathing problem such as chronic bronchitis
- persistent or chronic cough such as occurs with smoking, asthma chronic, bronchitis, or emphysema
- cough that occurs with too much phlegm (mucus)
- trouble urinating due to enlarged prostate gland

Ask a doctor or pharmacist before use if

You are taking the blood thinning drug warfarin

When using this product do not use more than directed

Stop use and ask a doctor if

- you get nervous, dizzy or sleepless
- symptoms do not get better within 7 days or are accompanied by fever
- cough comes back or occurs with fever, rash or persistant headache
- fever gets worse or lasts more than 3 days
- redness or swelling is present
- new symptoms occur. These could be signs of a serious condition.

If pregnant or breast-feeding

as a health professional before use

Keep out of reach of children

Overdose warning: Taking more than the recommended dose (overdose) may cause liver damage. In case of overdose, get medical help or contact a Poison Control Center right away. Quick medical attention is critical even if you do not notice any signs or symptoms.

Directions

- do not take more than directed
- Do not take more than 4 doses in any 24 hours
- This adult strength product is not intended for use in children under 12 years of age
- measure only with dosing cup provided
- keep dosing cup with product
- mL = mililiter
- dose as follows

age | dose
adults and children 12 years of age and older | 20 mL every 4 hours
children under 12 years of age | do not use

Other information

- Each 20 mL contains: sodium 10 mg
- store between15-30°C (59-86 °F), do not refrigerate

Inactive Ingredients

Anhydrous citric acid, edetate disodium, FD&C Blue # 1, FD&C Red # 40, flavors, glycerin, propylene glycol, propyl gallate, purified water, sodium benzoate, sorbitol, sucralose, xanthan gum

Questions or comments?

1-877-994-3666
Monday to Friday from 8 am to 6 pm, Central time

Tukol MAX ACTION Cold, Flu and Sore Throat

Tukol® MAX ACTION

DO NOT USE IF PRINTED SEAL UNDER CAP IS TORN OR MISSING

ACETAMINOPHEN/Dextromethorphan HBr/Guaifenesin/Phenylephrine HCl

Relieves

- Minor aches and Pain
- Fever
- Nasal & Chest Congestion
- Cough

Ages 12+
6 FL OZ (177 mL)

Distributed by:
Genomma Lab USA, Inc.
Houston, TX 77098